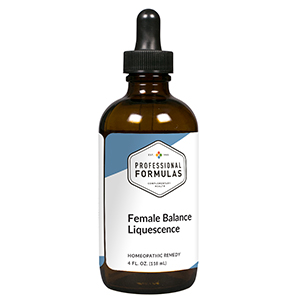 DRUG LABEL: Female Balance Liquescence
NDC: 63083-3009 | Form: LIQUID
Manufacturer: Professional Complementary Health Formulas
Category: homeopathic | Type: HUMAN OTC DRUG LABEL
Date: 20190815

ACTIVE INGREDIENTS: CHASTE TREE FRUIT 2 [hp_X]/118 mL; DIOSCOREA VILLOSA TUBER 2 [hp_X]/118 mL; GLYCYRRHIZA GLABRA 2 [hp_X]/118 mL; LIATRIS SPICATA ROOT 2 [hp_X]/118 mL; RUBUS IDAEUS FRUIT VOLATILE OIL 2 [hp_X]/118 mL; TRILLIUM ERECTUM ROOT 2 [hp_X]/118 mL; CAULOPHYLLUM THALICTROIDES ROOT 3 [hp_X]/118 mL; STRYCHNOS IGNATII SEED 3 [hp_X]/118 mL; SUS SCROFA MAMMARY GLAND 6 [hp_X]/118 mL; BOS TAURUS OVARY 6 [hp_X]/118 mL; SUS SCROFA UTERUS 6 [hp_X]/118 mL
INACTIVE INGREDIENTS: ALCOHOL; WATER

T9

ACTIVE INGREDIENTS

Agnus castus 2X
Dioscorea villosa 2X
Glycyrrhiza glabra 2X
Liatris spicata 2X
Rubus idaeus 2X
Trillium erectum 2X
Caulophyllum thalictroides 3X
Ignatia amara 3X
Mammary 6X
Ovary 6X
Uterus 6X

QUESTIONS

Professional Formulas

PO Box 2034 Lake Oswego, OR 97035

INDICATIONS

For the temporary relief of diminished sexual desire, tiredness or fatigue, sadness, nervousness, mild cramps, mild back pain, hot flashes, pain before menses, breast soreness, or periodic nausea.*

PURPOSE

*Claims based on traditional homeopathic practice, not accepted medical evidence. Not FDA evaluated.

WARNINGS

In case of overdose, get medical help or contact a poison control center right away.

Keep out of the reach of children.

PREGNANCY OR BREAST FEEDING

If pregnant or breastfeeding, ask a healthcare professional before use.

DIRECTIONS

Place drops under tongue 30 minutes before/after meals. Adults and children 12 years and over: Take one full dropper up to 2 times per day. Consult a physician for use in children under 12 years of age.

OTHER INFORMATION

Tamper resistant. If seal is broken, do not use. After opening, close container tightly and store at room temperature away from heat.

INACTIVE INGREDIENTS

20% ethanol, purified water.

LABEL

Est 1985

Professional Formulas

Complementary Health

Female Balance Liquescence

Homeopathic Remedy

4 FL. OZ. (118 mL)